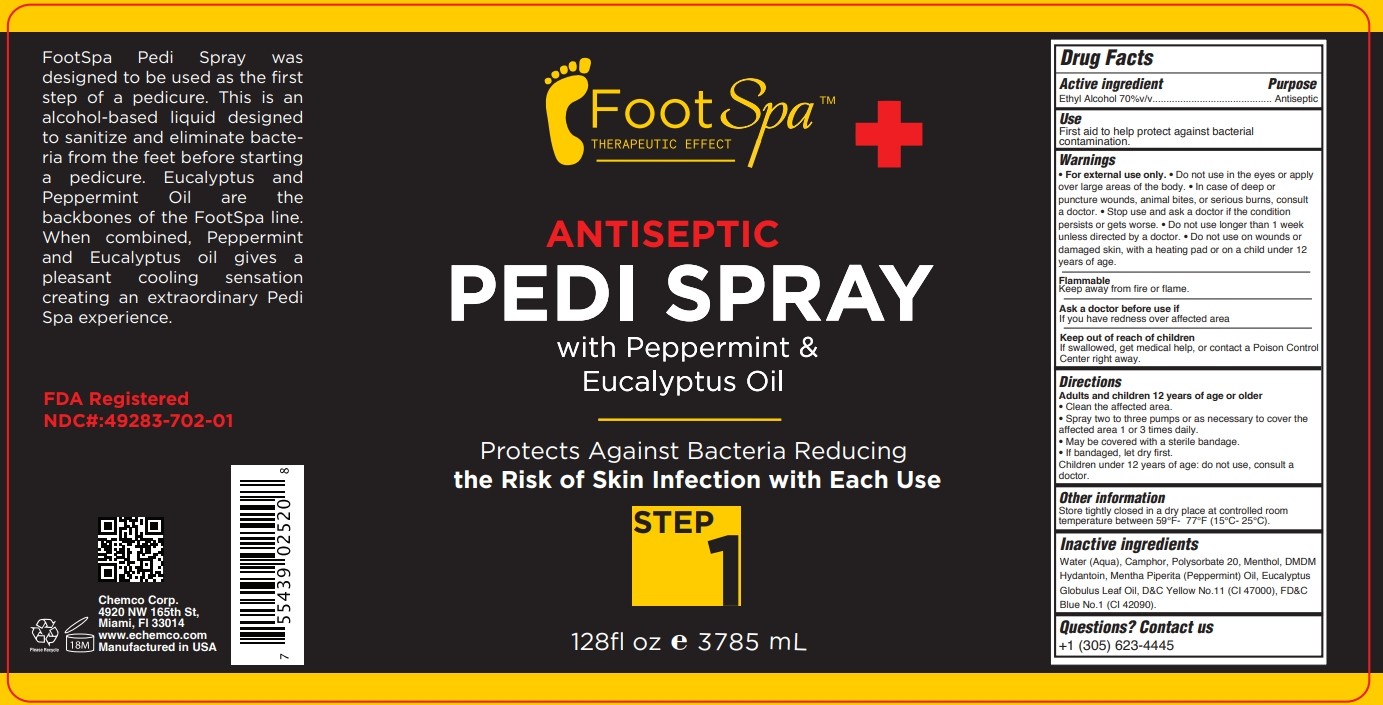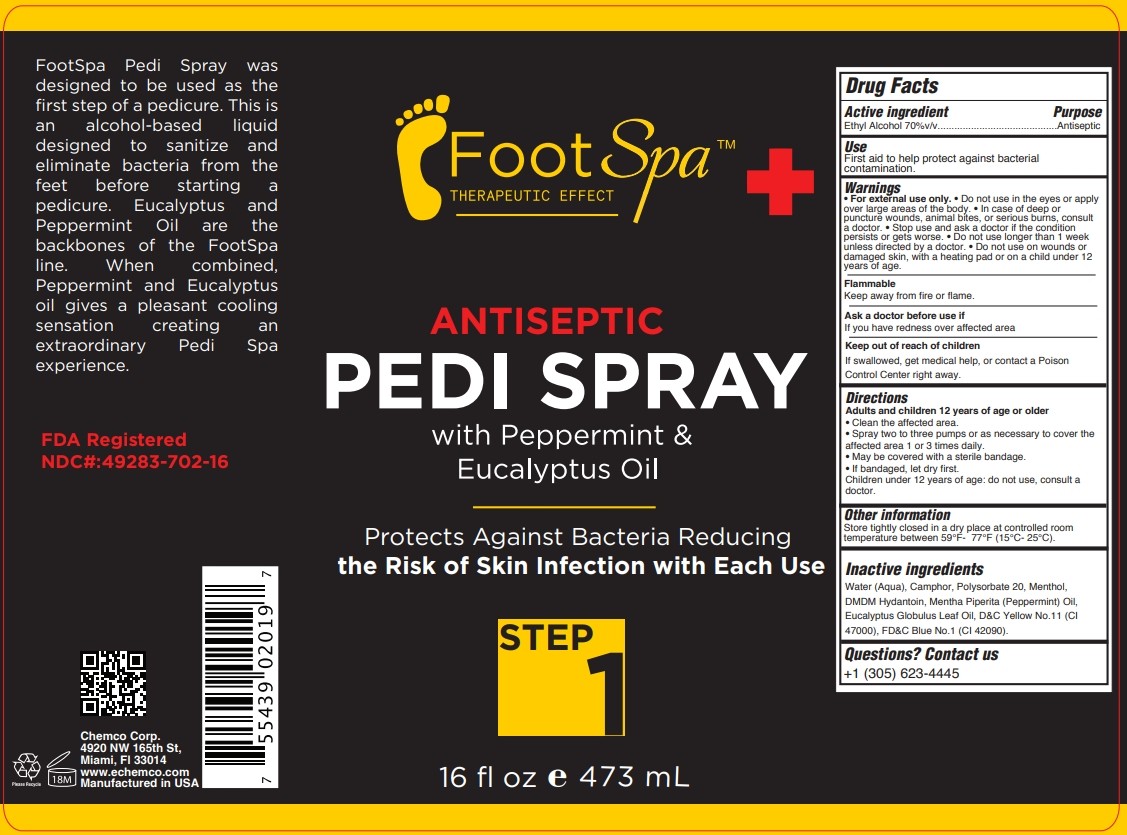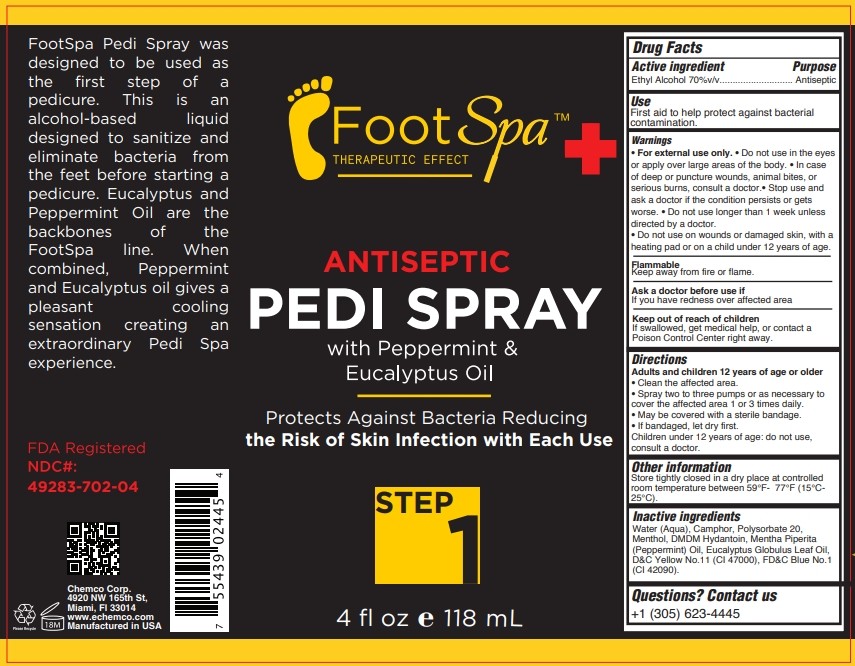 DRUG LABEL: FOOTSPA PEDI
NDC: 49283-702 | Form: SPRAY
Manufacturer: CHEMCO CORPORATION
Category: otc | Type: HUMAN OTC DRUG LABEL
Date: 20241113

ACTIVE INGREDIENTS: ALCOHOL 70 mL/100 mL
INACTIVE INGREDIENTS: WATER; POLYSORBATE 20; MENTHOL; FD&C BLUE NO. 1; CAMPHOR (SYNTHETIC); PEPPERMINT OIL; EUCALYPTUS OIL; D&C YELLOW NO. 11; DMDM HYDANTOIN

49283-702-16
49283-702-04
49283-702-01

ACTIVE INGREDIENT

Ethyl Alcohol 70%v/v

PURPOSE

Antiseptic

Uses

First aid to help protect against bacterial contamination.

WARNINGS

For external use only.

Do not use in the eyes or apply over large areas of the body.

In case of deep or puncture wounds, animal bites, or serious burns, consult a doctor.

Stop use and ask a doctor if the condition persists or gets worse.

Do not use longer than 1 week unless directed by a doctor.

For external use only.

Do not use on wounds or damaged skin, with a heating pad or on a child under 12 years of age

FLAMMABLE:

Keep away from fire or flame.

ASK A DOCTOR BEFORE USE IF

If you have redness over affected area.

KEEP OUT OF REACH OF CHILDREN

If swallowed, get medical help, or contact a Poison Control Center right away.

DIRECTIONS:

Adults and children 12 years of age or older

• Clean the affected area.

• Spray two to three pumps or as necessary to cover the affected area 1 or 3 times daily.

• May be covered with a sterile bandage.

• If bandaged, let dry first. Children under 12 years of age: do not use, consult a doctor.

INACTIVE INGREDIENT

Water (Aqua), Camphor, Polysorbate 20, Menthol, DMDM Hydantoin, Mentha Piperita (Peppermint) Oil, Eucalyptus Globulus Leaf Oil, D&C Yellow No.11(CI 47000), FD&C Blue No.1 (CI 42090).

QUESTIONS

Contact us
+1 (305) 623-4445